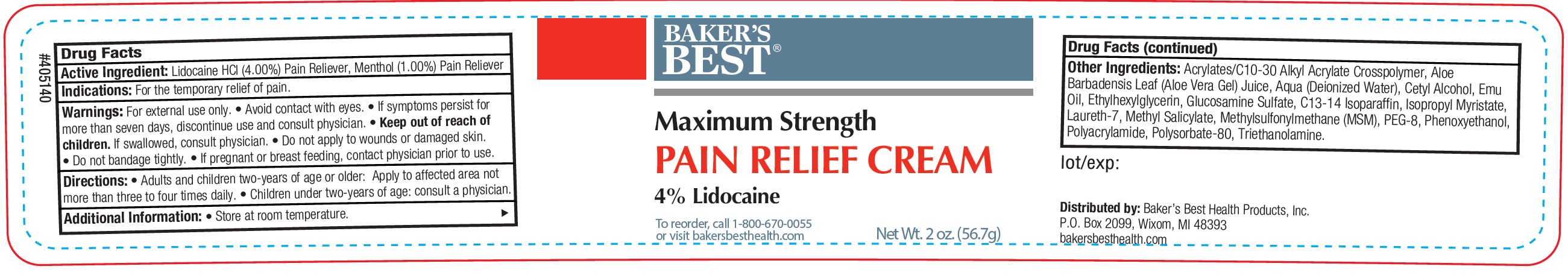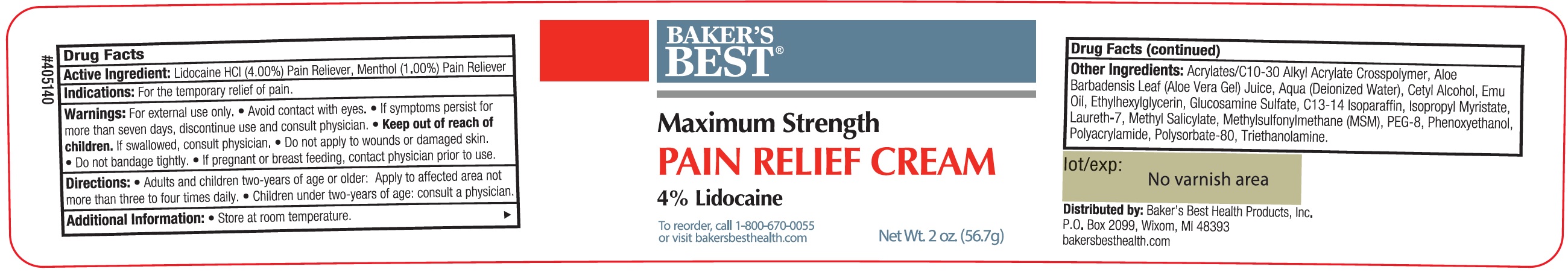 DRUG LABEL: Bakers Best Maximum Strength Pain Relief
NDC: 76102-031 | Form: CREAM
Manufacturer: Baker's Best Health Products, LLC
Category: otc | Type: HUMAN OTC DRUG LABEL
Date: 20231106

ACTIVE INGREDIENTS: LIDOCAINE HYDROCHLORIDE 40 mg/1 g; MENTHOL 10 mg/1 g
INACTIVE INGREDIENTS: CARBOMER INTERPOLYMER TYPE A (ALLYL SUCROSE CROSSLINKED); ALOE VERA LEAF; WATER; CETYL ALCOHOL; EMU OIL; ETHYLHEXYLGLYCERIN; GLUCOSAMINE SULFATE; C13-14 ISOPARAFFIN; ISOPROPYL MYRISTATE; LAURETH-7; METHYL SALICYLATE; DIMETHYL SULFONE; POLYETHYLENE GLYCOL 400; PHENOXYETHANOL; POLYSORBATE 80; TROLAMINE

Baker's Best Maximum Strength Pain Relief

Active Ingredient:

Lidocaine HCl (4.00%), Menthol (1.00%)

PURPOSE

Pain Reliever

Indications:

For the temporary relief of pain.

Warnings:

For external use only. • Avoid contact with eyes. • If symptoms persist for more than seven days, discontinue use and consult physician.

Keep out of reach of children.

If swallowed, consult physician.

Do not apply

- to wounds or damaged skin.
- Do not bandage tightly.

If pregnant or breast feeding,

contact physician prior to use.

Directions:

• Adults and children two-years of age or older: Apply to affected area not more than three to four times daily. • Children under two-years of age: consult a physician.

Additional Information:

• Store at room temperature.

Other Ingredients:

Acrylates/C10-30 Alkyl Acrylate Crosspolymer, Aloe Barbadensis Leaf (Aloe Vera Gel) Juice, Aqua (Deionize Water), Cetyl Alcohol, Emu Oil, Ethylhexylglycerin, Glucosamine Sulfate, C13-14 Isoparaffin, Isopropyl Myristate, Laureth-7, Methyl Salicylate, Methylsulfonylmethane (MSM), PEG-8, Phenoxyethanol, Polyacrylamide, Polysorbate-80, Triethanolamine.